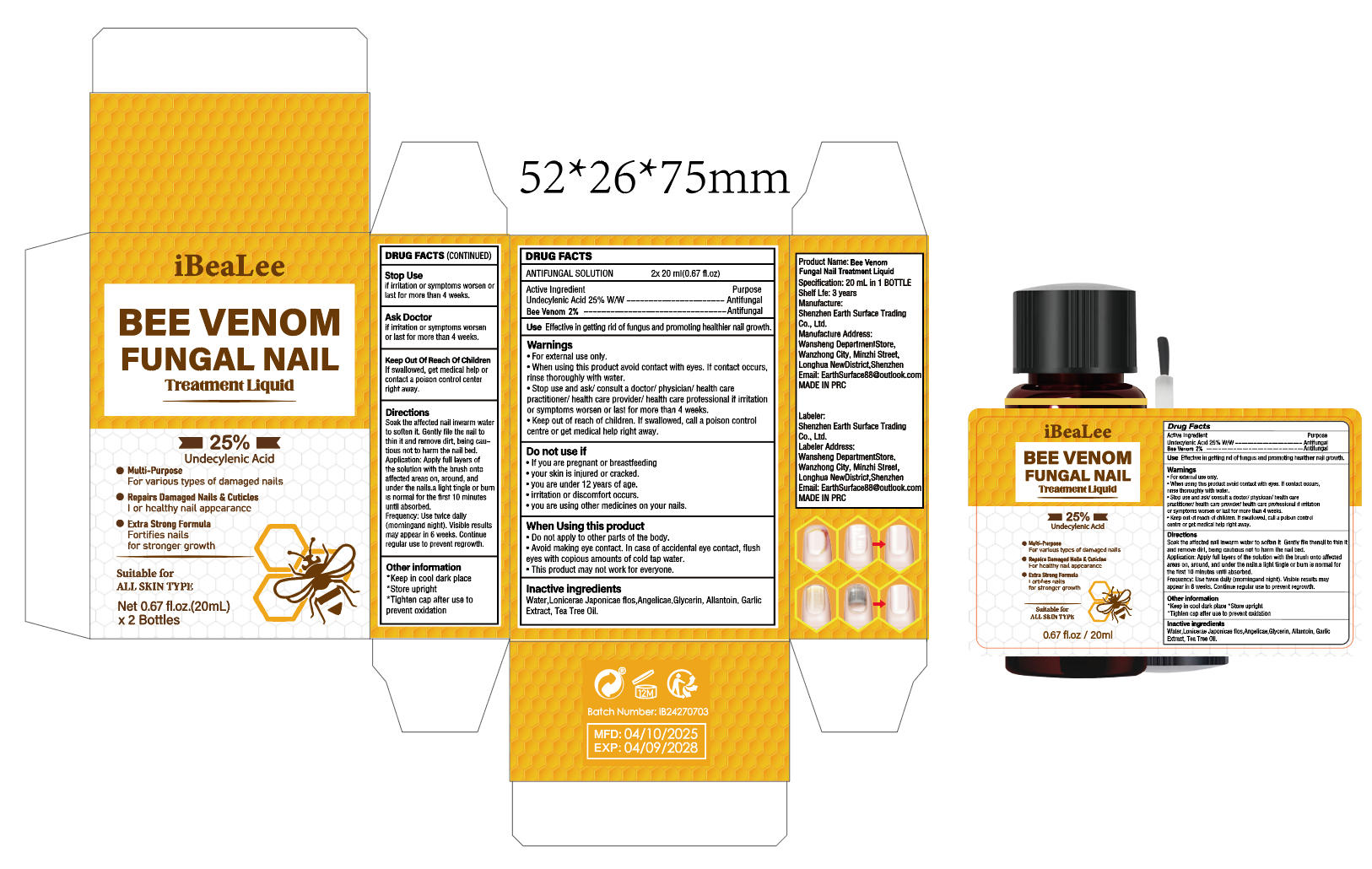 DRUG LABEL: Bee Venom Fungal Nail Treatment Liquid
NDC: 85636-012 | Form: LIQUID
Manufacturer: Shenzhen Earth Surface Trading Co., Ltd.
Category: otc | Type: HUMAN OTC DRUG LABEL
Date: 20260106

ACTIVE INGREDIENTS: UNDECYLENIC ACID 250 mg/1 mL
INACTIVE INGREDIENTS: APIS MELLIFERA VENOM; GARLIC; TEA TREE OIL; ANGELICA ACUTILOBA ROOT; ALLANTOIN; WATER; LONICERA JAPONICA FLOWER; GLYCERIN

Active ingredients

Undecylenic Acid 25% W/W

Bee Venom 2%

PURPOSE

Antifungal

Uses

Effective in getting rid of fungus and promoting healthier nail growth.

Warnings

• For external use only.
• When using this product avoid contact with eyes. If contact occurs,
rinse thoroughly with water.
• Stop use and ask/ consult a doctor/ physician/ health care
practitioner/ health care provider/ health care professional if irritation
or symptoms worsen or last for more than 4 weeks.
• Keep out of reach of children. If swallowed, call a poison control
centre or get medical help right away、

Stop use and ask a doctor if

if irritation or symptoms worsen
or last for more than 4 weeks.

Do not use

• If you are pregnant or breastfeeding
• your skin is injured or cracked.
• you are under 12 years of age.
• irritation or discomfort occurs.
• you are using other medicines on your nails.

When using this product

• Do not apply to other parts of the body.
• Avoid making eye contact. In case of accidental eye contact, flush
eyes with copious amounts of cold tap water.
• This product may not work for everyone.

Keep out of reach of children.

If swallowed, get medical help or contact a poison control center right away.

Inactive ingredients

Water,Lonicerae Japonicae flos,Angelicae,Glycerin, Allantoin, Garlic Extract, Tea Tree Oil.

Directions

Soak the affected nail inwarm water
to soften it. Gently file the nail to
thin it and remove dirt, being cau-
tious not to harm the nail bed.
Application: Apply full layers of
the solution with the brush onto
affected areas on, around, and
under the nails.a light tingle or burn
is normal for the first 10 minutes
until absorbed.
Frequency: Use twice daily
(morningand night). Visible results
may appear in 6 weeks. Continue
regular use to prevent regrowth.